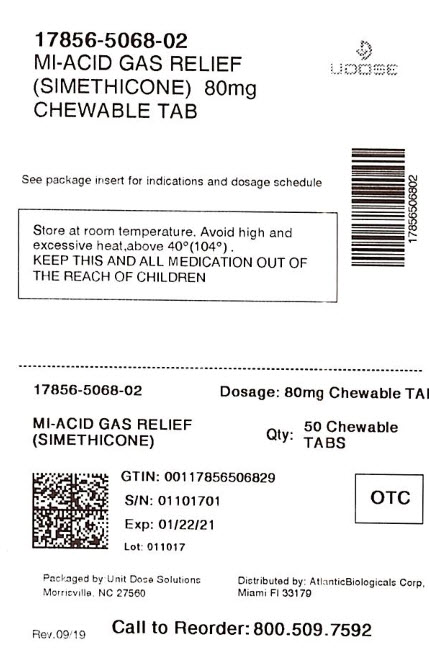 DRUG LABEL: Mi-Acid Gas Relief
NDC: 17856-5068 | Form: TABLET, CHEWABLE
Manufacturer: ATLANTIC BIOLOGICALS CORP.
Category: otc | Type: HUMAN OTC DRUG LABEL
Date: 20200722

ACTIVE INGREDIENTS: DIMETHICONE 80 mg/1 1
INACTIVE INGREDIENTS: SUCROSE; DEXTROSE, UNSPECIFIED FORM; MAGNESIUM STEARATE; MALTODEXTRIN; CELLULOSE, MICROCRYSTALLINE; SORBITOL

Mi-Acid Gas Relief

Active ingredient (in each tablet)

Simethicone 80 mg

Purpose

Antigas

Uses

relieves:

- pressure
- bloating
- symptoms referred to as gas

Warnings

Keep out of the reach of children. In case of overdose, get medical help or contact a poison control center immediately.

Directions

- chew 2 to 4 tablets thoroughly as needed after meals and at bedtime.
- do not exceed 6 tablets per day unless directed by a physician.

Other information

- do not use if inner seal is broken.
- store at room temperature
- avoid high humidity and excessive heat, above 40^0C (104^0F)

Inactive ingredients

compressible sugar, dextrose, flavor, magnesium stearate, maltodextrin, microcrystalline cellulose, sorbitol

Questions or comments?

Call (800) 616-2471

DISTRIBUTED BY:

ATLANTIC BIOLOGICALS CORP.

MIAMI, FL 33179

PDP

NDC 17856-5068-2

Mi-Acid Gas Relief

Relieves Gas Pain, Pressure and Bloating

Simethicone 80 mg/Antiflatulent

100 Chewable Tablets